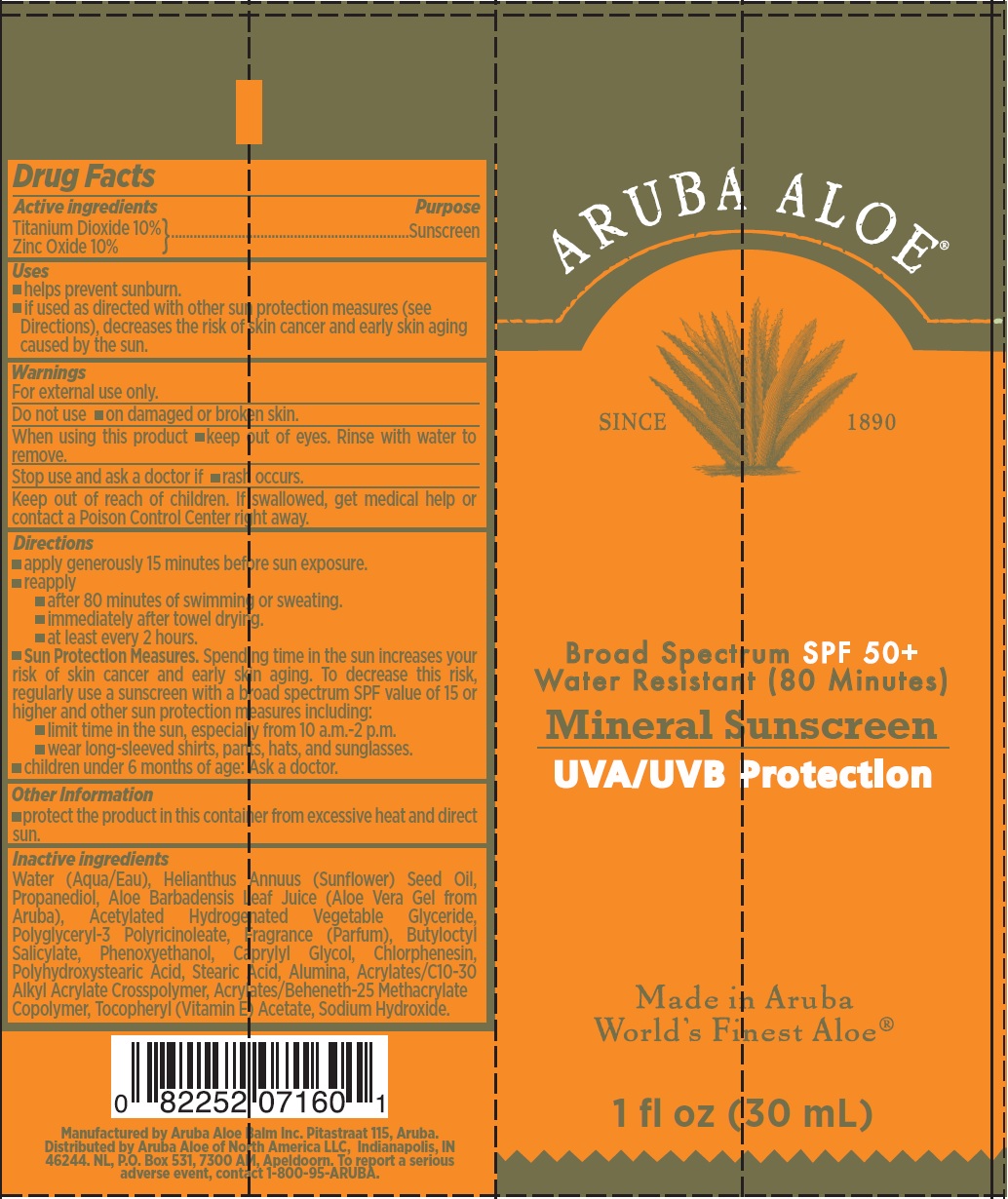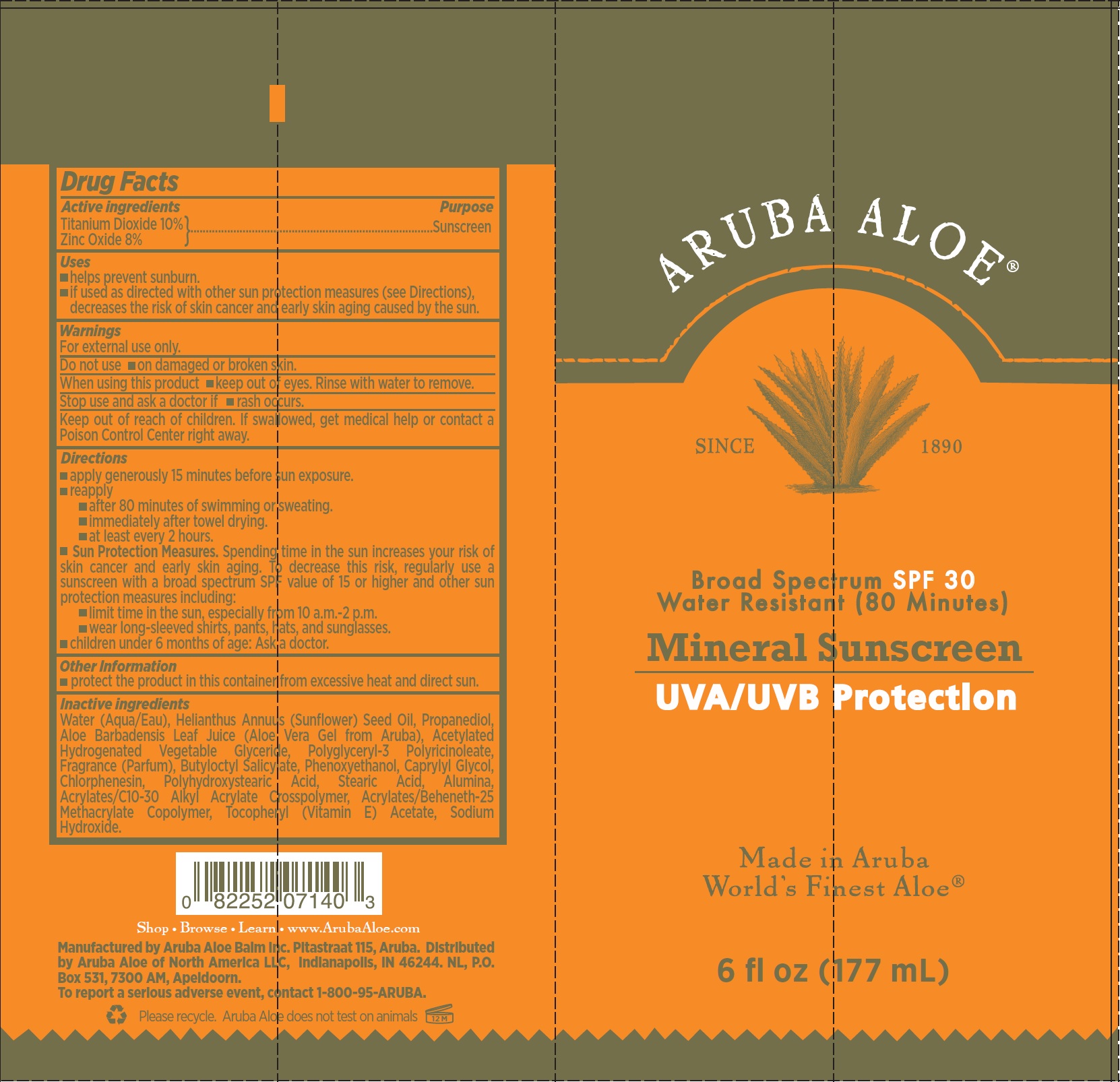 DRUG LABEL: Aruba Aloe Broad Spectrum SPF 30 Mineral Sunscreen
NDC: 53675-182 | Form: CREAM
Manufacturer: Aruba Aloe Balm NV
Category: otc | Type: HUMAN OTC DRUG LABEL
Date: 20250207

ACTIVE INGREDIENTS: TITANIUM DIOXIDE 100 mg/1 mL; ZINC OXIDE 80 mg/1 mL
INACTIVE INGREDIENTS: WATER; SUNFLOWER OIL; PROPANEDIOL; ALOE VERA LEAF; BUTYLOCTYL SALICYLATE; PHENOXYETHANOL; CAPRYLYL GLYCOL; CHLORPHENESIN; STEARIC ACID; ALUMINUM OXIDE; SODIUM HYDROXIDE

Aruba Aloe Broad Spectrum SPF 30 Mineral Sunscreen

Active ingredients

Titanium Dioxide 10%
Zinc Oxide 8%

Purpose

Sunscreen

Uses

- helps prevent sunburn.
- if used as directed with other sun protection measures (see Directions), decreases the risk of skin cancer and early skin aging caused by the sun.

Warnings

For external use only.

Do not use

- on damaged or broken skin.

When using this product

- keep out of eyes. Rinse with water to remove.

Stop use and ask a doctor if

- rash occurs.

Keep out of reach of children.

If swallowed, get medical help or contact a Poison Control Center right away.

Directions

- apply generously 15 minutes before sun exposure.
- reapply
- after 80 minutes of swimming or sweating.
- immediately after towel drying.
- at least every 2 hours.
- Sun Protection Measures. Spending time in the sun increases your risk of skin cancer and early skin aging. To decrease this risk, regularly use a sunscreen with a broad spectrum SPF value of 15 or higher and other sun protection measures including:
- limit time in the sun, especially from 10 a.m.-2 p.m.
- wear long-sleeved shirts, pants, hats, and sunglasses.
- children under 6 months of age: Ask a doctor.

Other Information

- protect the product in this container from excessive heat and direct sun.

Inactive ingredients

Water (Aqua/Eau), Helianthus Annuus (Sunflower) Seed Oil, Propanediol, Aloe Barbadensis Leaf Juice (Aloe Vera Gel from Aruba), Acetylated Hydrogenated Vegetable Glyceride, Polyglyceryl-3 Polyricinoleate, Fragrance (Parfum), Butyloctyl Salicylate, Phenoxyethanol, Caprylyl Glycol, Chlorphenesin, Polyhydroxystearic Acid, Stearic Acid, Alumina, Acrylates/C10-30 Alkyl Acrylate Crosspolymer, Acrylates/Beheneth-25 Methacrylate Copolymer, Tocopheryl (Vitamin E) Acetate, Sodium Hydroxide.